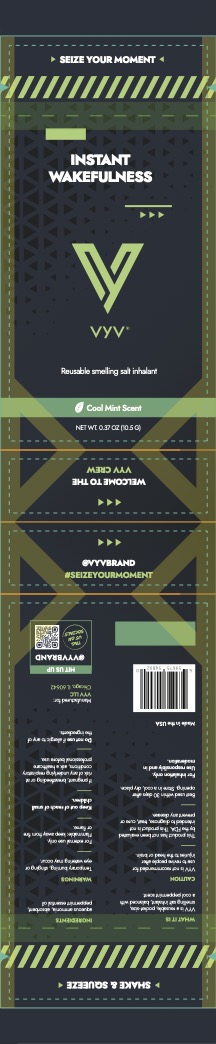 DRUG LABEL: VYV Smelling Salts
NDC: 85771-101 | Form: INHALANT
Manufacturer: VYV LLC
Category: otc | Type: HUMAN OTC DRUG LABEL
Date: 20250604

ACTIVE INGREDIENTS: AMMONIA 29 g/100 g
INACTIVE INGREDIENTS: PEPPERMINT OIL; SODIUM POLYACRYLATE (8000 MW)

ACTIVE INGREDIENT

Aqueous ammonia (29%)

PURPOSE

Reflex stimulant

INDICATIONS AND USAGE

Respitory stimulant. For inhalation only. Use responsibly and in moderation.

Best used within 30 days after opening. Store in a cool, dry place

WARNINGS

- Temporary burning, stinging or eye watering may occur.
- For external use only. Flammable: keep away from fire or flame.
- Do not use if allergic to any of the ingredients.
- Not recommended for use to revive people after injuries to the head or brain.
- This product has not been evaluated by the FDA. This product is not intended to diagnose, treat, cure or prevent any disease

Keep out of reach of small children.

PREGNANCY OR BREAST FEEDING

If pregnant, breastfeeding or at risk of any underlying respiratory conditions, ask a healthcare professional before use.

DOSAGE AND ADMINISTRATION

1. Hold 2-3 inches below nose
2. Squeeze & inhale

INACTIVE INGREDIENT

Peppermint essential oil, sodium polyacrylate